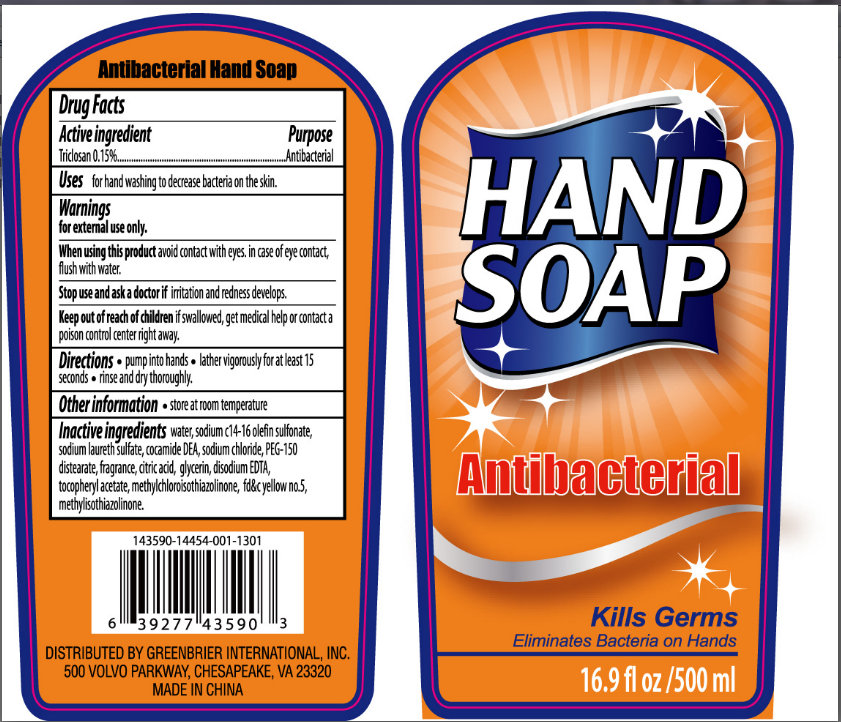 DRUG LABEL: Antibacterial Hand
NDC: 33992-0100 | Form: SOAP
Manufacturer: Greenbrier International, Inc.
Category: otc | Type: HUMAN OTC DRUG LABEL
Date: 20121205

ACTIVE INGREDIENTS: TRICLOSAN 1.5 mg/1 mL
INACTIVE INGREDIENTS: WATER; SODIUM C14 OLEFIN SULFONATE; SODIUM LAURETH-3 SULFATE; COCO DIETHANOLAMIDE; SODIUM CHLORIDE; PEG-150 DISTEARATE; CITRIC ACID MONOHYDRATE; GLYCERIN; EDETATE DISODIUM; .ALPHA.-TOCOPHEROL ACETATE; METHYLCHLOROISOTHIAZOLINONE; FD&C YELLOW NO. 5; METHYLISOTHIAZOLINONE

Antibacterial Hand Soap

Active Ingredient

Triclosan 0.15%

Purpose

Antibacterial

Uses

For hand washing to decrease bacteria on the skin.

Warnings

For external use only.

When using this product avoid contact with eyes. In case of contact, flush with water.

Stop use and ask a doctor if irritation and redness develops.

Keep out of reach of children if swallowed, get medical help or contact a poison control center right away.

Directions

- pump into hands
- lather vigorously for at least 15 seconds
- rinse and dry thoroughly

Other Information

- store at room temperature

Inactive Ingredients

water, sodium c14-16 olefin sulfonate, sodium laureth sulfate, cocamide DEA, sodium chloride, PEG-150 distearate, fragrance, citric acid, glycerin, disodium EDTA, tocopheryl acetate, methylchloroisothiazolinone, fd c yellow no.5, methylisothiazolinone.